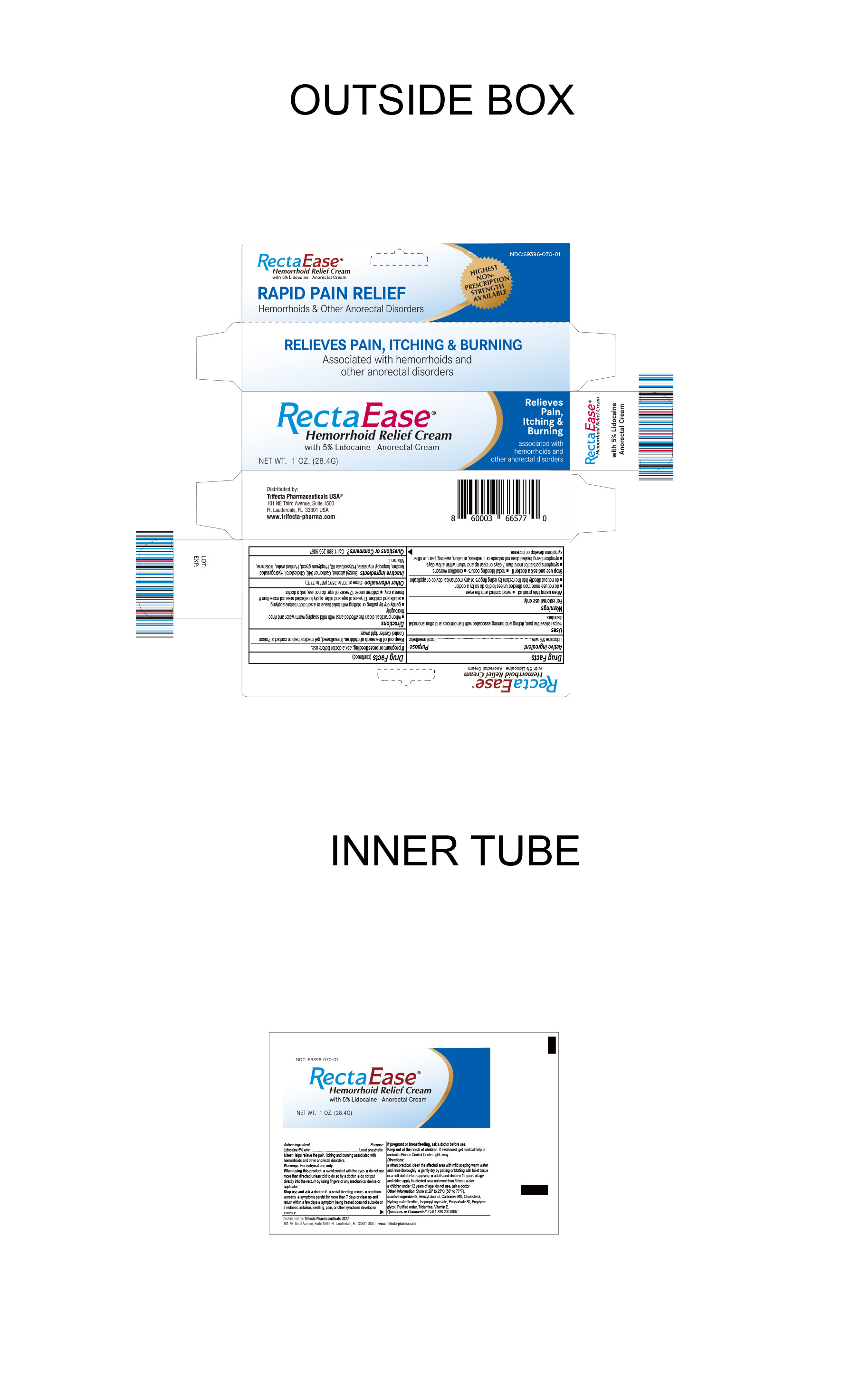 DRUG LABEL: RectaEase Hemorrhoid Relief Cream
NDC: 69396-070 | Form: CREAM
Manufacturer: Trifecta Pharmaceuticals USA LLC
Category: otc | Type: HUMAN OTC DRUG LABEL
Date: 20251208

ACTIVE INGREDIENTS: LIDOCAINE 50 mg/1 g
INACTIVE INGREDIENTS: POLYSORBATE 80; BENZYL ALCOHOL; PROPYLENE GLYCOL; WATER; ALPHA-TOCOPHEROL ACETATE; CHOLESTEROL; ISOPROPYL MYRISTATE; LIGHT MINERAL OIL; ALOE BARBADENSIS LEAF JUICE; CARBOMER HOMOPOLYMER, UNSPECIFIED TYPE; SODIUM HYDROXIDE

RectaEase Hemorrhoid Relief Cream

Active Ingredient

Lidocaine 5% w/w

Purpose

Local Anesthetic

Uses

Helps relieve the pain, ithcing and burning associated with hemorrhoids and other anorectal disorders.

Warning Section

For External Use Only

Stop use and ask a doctor

Rectal bleeding occurs

Condition worsens

Symptoms persist for more than 7 days or clear up and return within a few days

Symptoms being treated does not subside or if redness, irritation, swelling, pain or other symptoms develop or increase.

When using this product

Avoid contact with the eyes

do not use more than directed unless told to do so by a doctor

do not put directly into the rectum by using fingers or any mechanical device or applicator

If Pregnant or Breast Feeding

Ask doctor before use

Keep out of reach of children

If swallowed get medical help or contact a Poison Control Center right away

Directions

When practical, clean the affected area with mild soaping warm water and rinse thoroughly.

Gently dry by patting or blotting with a toilet tissue or soft cloth before applying.

Adult and children 12 years of age and older, apply to affected area not more than 6 times a day.

Children under 12 years of age: do not use, ask a doctor

Other Information

Store at 20º-25ºC (68º-77ºF)

Inactive Ingredients

Benzyl alcohol, Carbomer 940, Cholesterol, Hydrogenated Lecithin, Isopropyl myristate, Propylene glycol,Trolamine, Vitamin E, polysorbate 80, propylene glycol, purified water

Questions or Comments

Call 1-888-296-9067

Distributed By

Trifecta Pharmaceuticals USA™

101 NE Third Avenue, Suite 1500

Ft. Lauderdale, FL. 33301, USA

1-888-296-9067

www.trifecta-pharma.com